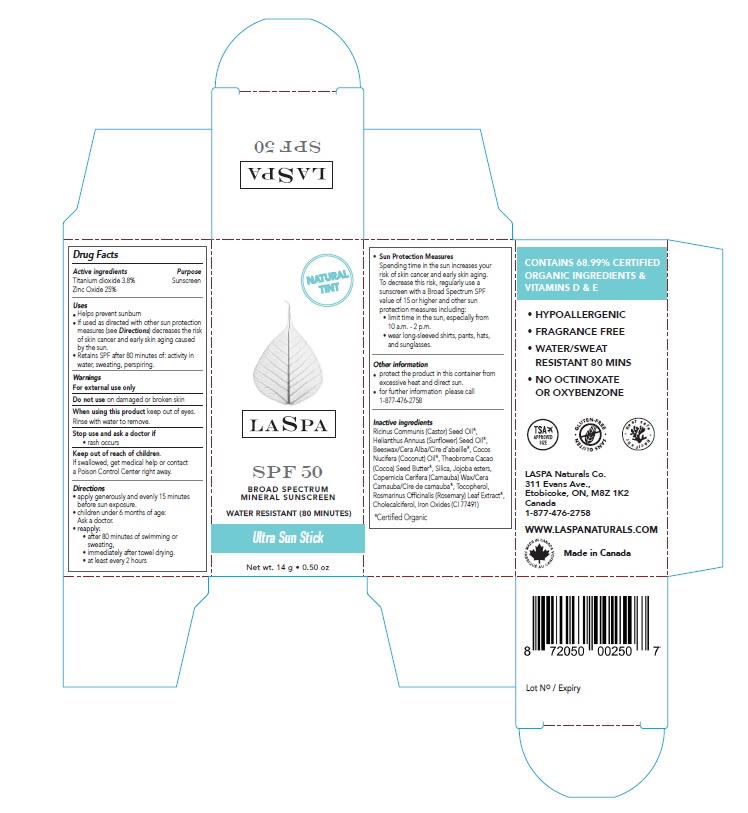 DRUG LABEL: LASPA BROAD SPECTRUM MINERAL SUNSCREEN SPF 50 ULTRA SUN
NDC: 71780-550 | Form: STICK
Manufacturer: The Green Cricket Inc
Category: otc | Type: HUMAN OTC DRUG LABEL
Date: 20210623

ACTIVE INGREDIENTS: TITANIUM DIOXIDE 38 mg/1 g; ZINC OXIDE 250 mg/1 g
INACTIVE INGREDIENTS: CHOLECALCIFEROL; TOCOPHEROL; YELLOW WAX; SUNFLOWER OIL; COCONUT OIL; COCOA BUTTER; SILICON DIOXIDE; CARNAUBA WAX; CASTOR OIL; HYDROGENATED JOJOBA OIL, RANDOMIZED; FERRIC OXIDE RED; ROSEMARY

LASPA BROAD SPECTRUM MINERAL SUNSCREEN SPF 50 ULTRA SUN STICK

Active ingredients

Titanium dioxide 3.8%

Zinc Oxide 25%

Purpose

Sunscreen

Uses

- Helps prevent sunburn
- If used as directed with other sun protection measures (see Directions) decreases the risk of skin cancer and early skin aging caused by the sun.
- Retains SPF after 80 minutes of: activity in water, sweating, perspiring.

Warnings

For external use only

Do not use

on damaged or broken skin

When using this product

keep out of eyes. Rinse with water to remove.

Stop use and ask a doctor if

rash occurs

Keep out of reach of children.

If swallowed, get medical help or contact a Poison Control Center right away.

Directions

- apply generously and evenly 15 minutes before sun exposure.
- children under 6 months of age: Ask a doctor.
- reapply:
- after 80 minutes of swimming or sweating,
- immediately after towel drying.
- at least every 2 hours
- Sun Protection Measures: Spending time in the sun increases your risk of skin cancer and early skin aging. To decrease this risk, regularly use a sunscreen with a Broad Spectrum SPF value of 15 or higher and other sun protection measures including:
- limit time in the sun, especially from 10 a.m. - 2 p.m.
- wear long-sleeved shirts, pants, hats, and sunglasses.

Other information

- protect the product in this container from excessive heat and direct sun.
- for further information please call 1-877-476-2758

Inactive ingredients

Ricinus Communis (Castor) Seed Oil*, Helianthus Annuus (Sunflower) Seed Oil*, Beeswax/Cera Alba/Cire d'abeille*, Cocos Nucifera (Coconut) Oil*, Theobroma Cacao (Cocoa) Seed Butter*, Silica, Jojoba esters, Copernicia Cerifera (Carnauba) Wax/Cera Carnauba/Cire de carnauba*, Tocopherol, Rosmarinus Officinalis (Rosemary) Leaf Extract*, Cholecalciferol, Iron Oxides (CI 77491)

*Certified Organic

Company Information

LASPA Naturals Co.

311 Evans Ave.,

Etobicoke, ON, M8Z 1K2

1-877-476-2758